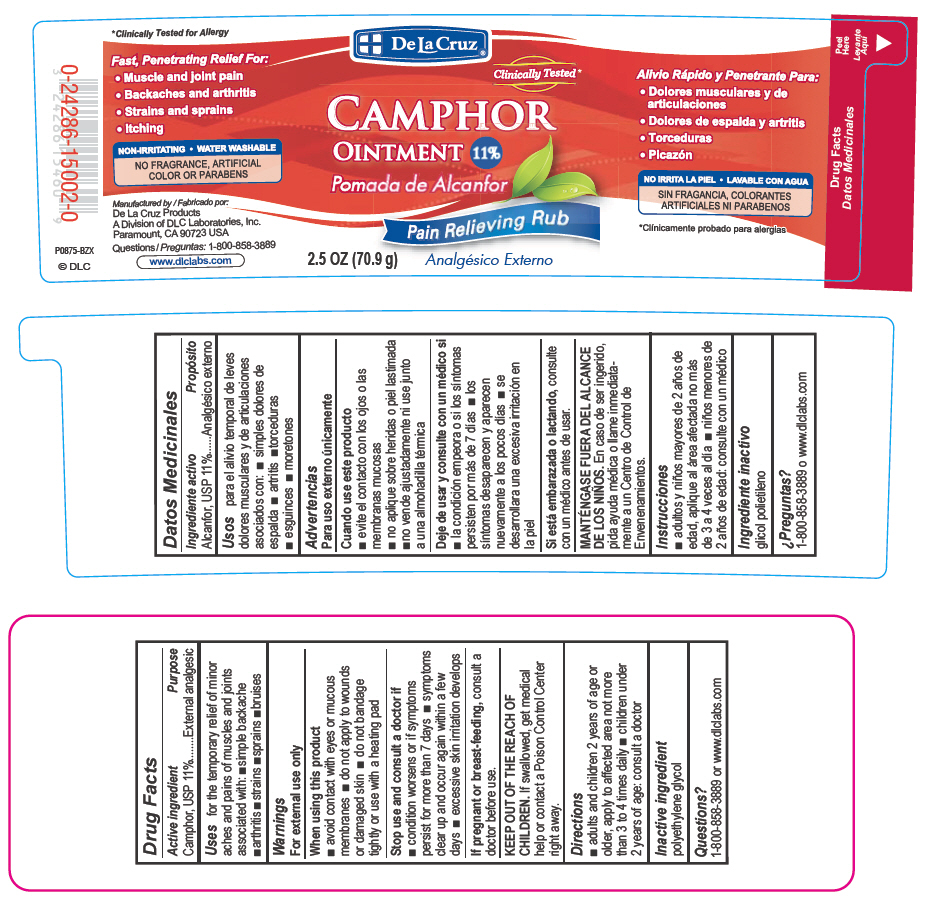 DRUG LABEL: De La Cruz Camphor
NDC: 24286-1521 | Form: OINTMENT
Manufacturer: DLC Laboratories, Inc.
Category: otc | Type: HUMAN OTC DRUG LABEL
Date: 20241010

ACTIVE INGREDIENTS: CAMPHOR (SYNTHETIC) 11 g/100 g
INACTIVE INGREDIENTS: POLYETHYLENE GLYCOL, UNSPECIFIED

CAMPHOR Ointment 11%

Active Ingredient

Camphor, USP 11%

Purpose

External analgesic

Uses

for the temporary relief of minor aches and pains of muscles and joints associated with simple backache, arthritis, strains, bruises and sprains

Warnings

For external use only

When using this product

avoid contact with eyes or mucous membranes

do not apply to wounds or damaged skin

do not bandage tightly or use with a heating pad

Stop use and consult a doctor if

condition worsens or if symptoms persist for more than 7 days

symptoms clear up and occur again within a few days.

excessive skin irritation develops

If pregnant or breastfeeding,

consult a doctor before use.

KEEP OUT OF THE REACH OF CHILDREN.

If swallowed, get medical help or contact a Poison Control Center right away.

Directions

adults and children 2 years of age or older, apply to affected area not more than 3 to 4 times daily

children under 2 years of age: consult a doctor

Inactive ingredient

polyethylene glycol

Questions?

1-800-858-3889 or www.dlclabs.com

De La Cruz

CAMPHOR
Ointment 11%

Pain relieving rub

2.5 OZ (70.9g)

FAST, PENETRATING RELIEF FOR:

Muscle and joint pain

Backaches and arthritis

Strains and sprains

Itching

NON-IRRITATING
WATER WASHABLE
NO PARABENS OR ARTIFICIAL FRAGRANCES OR COLORS

Manufactured by:

De La Cruz Products

A Division of DLC Laboratories, Inc.

Paramount, CA 90723 USA

Questions: 1-800-858-3889

www.dlclabs.com (c) DLC

PRINCIPAL DISPLAY PANEL - 70.9 g Jar Label

De La Cruz®

Clinically Tested*

CAMPHOR
OINTMENT 11%

Pain Relieving Rub

2.5 OZ (70.9 g)